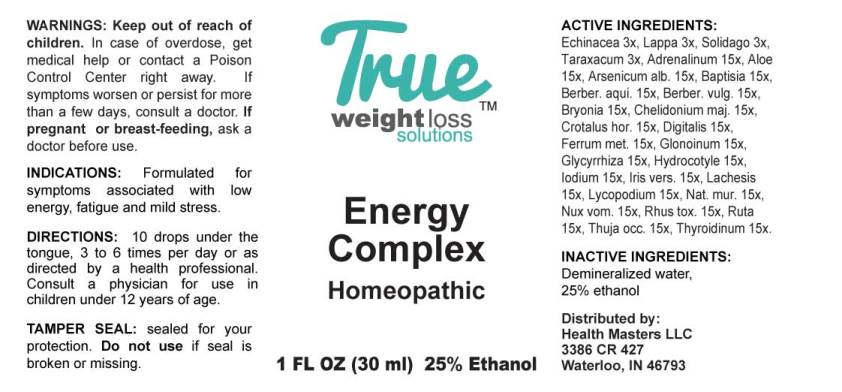 DRUG LABEL: Energy Complex
NDC: 73162-0003 | Form: LIQUID
Manufacturer: Health Masters LLC
Category: homeopathic | Type: HUMAN OTC DRUG LABEL
Date: 20240122

ACTIVE INGREDIENTS: ECHINACEA ANGUSTIFOLIA WHOLE 3 [hp_X]/1 mL; ARCTIUM LAPPA ROOT 3 [hp_X]/1 mL; SOLIDAGO VIRGAUREA FLOWERING TOP 3 [hp_X]/1 mL; TARAXACUM OFFICINALE 3 [hp_X]/1 mL; EPINEPHRINE 15 [hp_X]/1 mL; ALOE 15 [hp_X]/1 mL; ARSENIC TRIOXIDE 15 [hp_X]/1 mL; BAPTISIA TINCTORIA ROOT 15 [hp_X]/1 mL; MAHONIA AQUIFOLIUM ROOT BARK 15 [hp_X]/1 mL; BERBERIS VULGARIS ROOT BARK 15 [hp_X]/1 mL; BRYONIA ALBA ROOT 15 [hp_X]/1 mL; CHELIDONIUM MAJUS WHOLE 15 [hp_X]/1 mL; CROTALUS HORRIDUS HORRIDUS VENOM 15 [hp_X]/1 mL; DIGITALIS 15 [hp_X]/1 mL; IRON 15 [hp_X]/1 mL; NITROGLYCERIN 15 [hp_X]/1 mL; GLYCYRRHIZA GLABRA 15 [hp_X]/1 mL; CENTELLA ASIATICA 15 [hp_X]/1 mL; IODINE 15 [hp_X]/1 mL; IRIS VERSICOLOR ROOT 15 [hp_X]/1 mL; LACHESIS MUTA VENOM 15 [hp_X]/1 mL; LYCOPODIUM CLAVATUM SPORE 15 [hp_X]/1 mL; SODIUM CHLORIDE 15 [hp_X]/1 mL; STRYCHNOS NUX-VOMICA SEED 15 [hp_X]/1 mL; TOXICODENDRON PUBESCENS LEAF 15 [hp_X]/1 mL; RUTA GRAVEOLENS FLOWERING TOP 15 [hp_X]/1 mL; THUJA OCCIDENTALIS LEAFY TWIG 15 [hp_X]/1 mL; THYROID, BOVINE 15 [hp_X]/1 mL
INACTIVE INGREDIENTS: WATER; ALCOHOL

DRUG FACTS:

ACTIVE INGREDIENTS:

Echinacea (Angustifolia) 3x, Lappa Major 3x, Solidago Virgaurea 3x, Taraxacum Officinale 3x, Adrenalinum 15x, Aloe 15x, Arsenicum Album 15x, Baptisia Tinctoria 15x, Berberis Aquifolium 15x, Berberis Vulgaris 15x, Bryonia (Alba) 15x, Chelidonium Majus 15x, Crotalus Horridus 15x, Digitalis Purpurea 15x, Ferrum Metallicum 15x, Glonoinum 15x, Glycyrrhiza Glabra 15x, Hydrocotyle Asiatica 15x, Iodium 15x, Iris Versicolor 15x, Lachesis Mutus 15x, Lycopodium Clavatum 15x, Natrum Muriaticum 15x, Nux Vomica 15x, Rhus Tox 15X, Ruta Graveolens 15x, Thuja Occidentalis 15x, Thyroidinum (Bovine) 15x.

INDICATIONS:

Formulated for symptoms associated with low energy, fatigue and mild stress.

WARNINGS:

Keep out of reach of children. In case of overdose, get medical help or contact a Poison Control Center right away.

If symptoms worsen or persist for more than a few days, consult a doctor.

If pregnant or breast-feeding, ask a doctor before use.

TAMPER SEAL: sealed for your protection. Do not use if seal is broken or missing.

Keep out of reach of children. In case of overdose, get medical help or contact a Poison Control Center right away.

DIRECTIONS:

10 drops under the tongue, 3 to 6 times per day or as directed by a health professional. Consult a physician for use in children under 12 years of age.

INDICATIONS:

Formulated for symptoms associated with low energy, fatigue and mild stress.

INACTIVE INGREDIENTS:

Demineralized water, 25% ethanol.

QUESTIONS:

Distributed by:

Health Masters LLC

3386 CR 427

Waterloo, IN 46793

PACKAGE LABEL DISPLAY:

TRUE
weight loss
solutions
Energy
Complex
Homeopathic
1 FL OZ (30 ml)